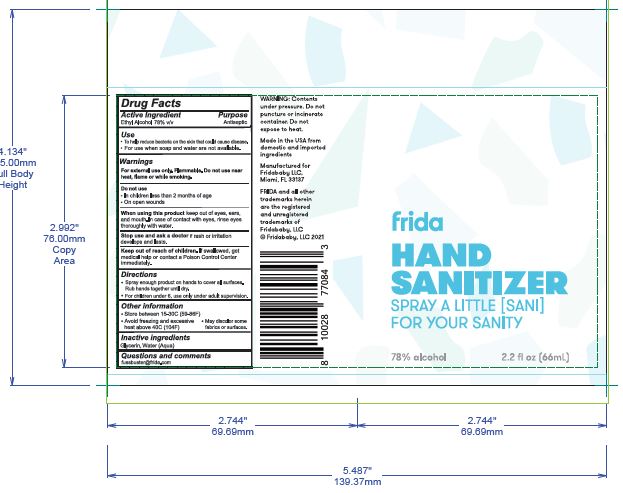 DRUG LABEL: Hand Sanitizer
NDC: 72686-183 | Form: AEROSOL, SPRAY
Manufacturer: Fareva Morton Grove, Inc.
Category: otc | Type: HUMAN OTC DRUG LABEL
Date: 20201203

ACTIVE INGREDIENTS: ALCOHOL 78 mL/100 mL
INACTIVE INGREDIENTS: GLYCERIN; WATER

1. Alcohol (ethanol) (USP or Food Chemical Codex (FCC) grade) (78%, volume/volume (v/v)) in an aqueous solution denatured according to Alcohol and Tobacco Tax and Trade Bureau regulations in 27 CFR part 20.
2. Glycerin
3. Sterile distilled water or boiled cold water.

.

Active Ingredient(s)

Alcohol 78% v/v. Purpose: Antiseptic

Purpose

Antiseptic, Hand Sanitizer

Use

To help reduce bacteria that potentially can cause disease. For use when soap and water are not available.

Warnings

For external use only. Flammable. Keep away from heat or flame

Do not use

- in children less than 2 months of age
- on open skin wounds

When using this product keep out of eyes, ears, and mouth. In case of contact with eyes, rinse eyes thoroughly with water.
Stop use and ask a doctor if irritation or rash develops and lasts.
Keep out of reach of children. If swallowed, get medical help or contact a Poison Control Center right away.

Stop use and ask a doctor if irritation or rash develops and lasts.

Keep out of reach of children. If swallowed, get medical help or contact a Poison Control Center right away.

Directions

- Spray enough product on hands to cover all surfaces. Rub hands together until dry.
- For children under 6, use only under adult supervision.

RECENT MAJOR CHANGES

Updated due to product being an aerosol

Other information

- Store between 15-30C (59-86F)
- Avoid freezing and excessive heat above 40C (104F)

Inactive ingredients

glycerin, water

Package Label - Principal Display Panel

66 mL NDC: 72686-183-10

fridababy_2oz_BOV.jpg